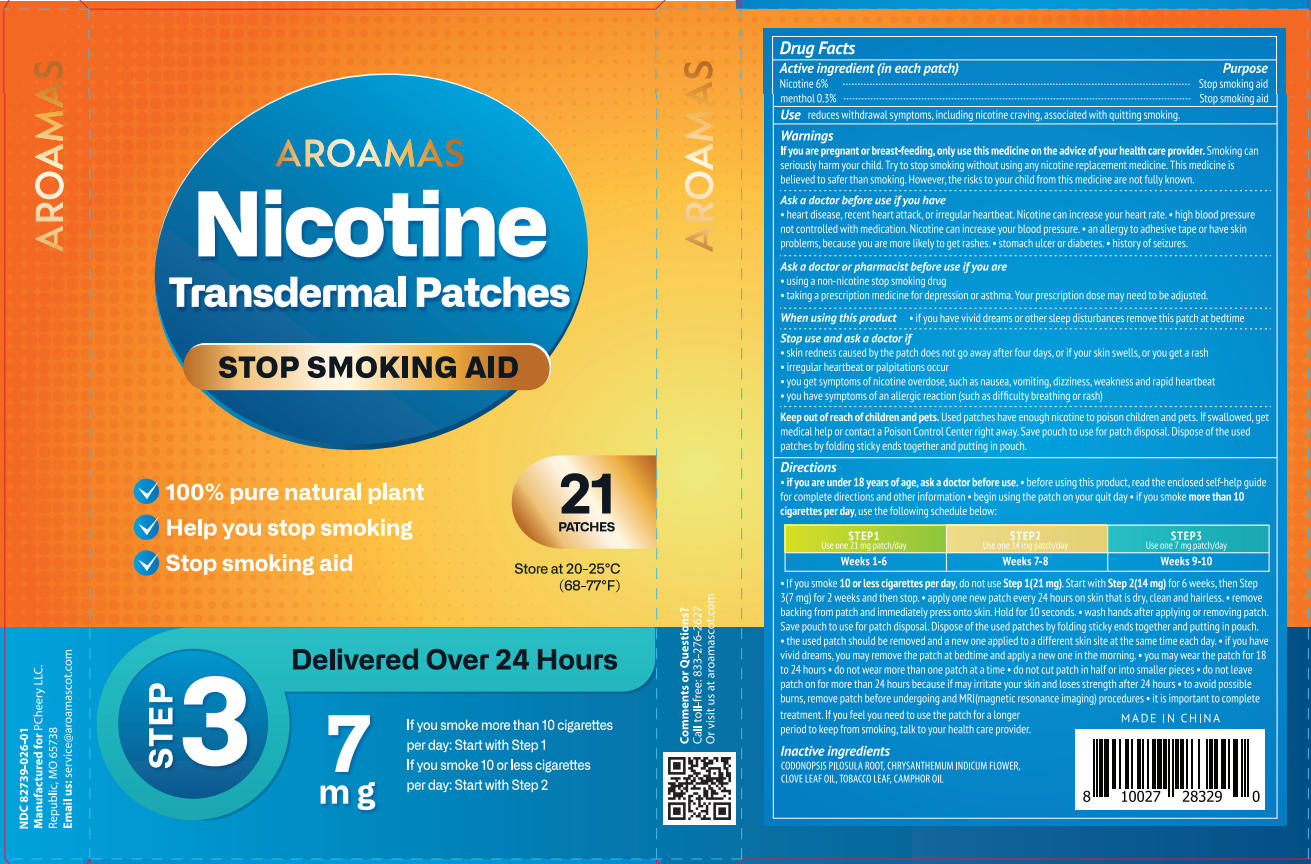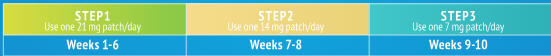 DRUG LABEL: AROAMAS COT NICOTINE TRANSDERMAL PATCHES STEP 3
NDC: 85831-035 | Form: PATCH
Manufacturer: PCHEERY LLC
Category: otc | Type: HUMAN OTC DRUG LABEL
Date: 20251209

ACTIVE INGREDIENTS: MENTHOL 0.3 g/100 1; NICOTINE 6 g/100 1
INACTIVE INGREDIENTS: CODONOPSIS PILOSULA ROOT; TOBACCO LEAF; CLOVE LEAF OIL; CAMPHOR OIL; CHRYSANTHEMUM INDICUM FLOWER

Initial Drug Listing - AROAMAS COT NICOTINE TRANSDERMAL PATCHES STEP 3

ACTIVE INGREDIENT

Nicotine 6%

Menthol 0.3%

PURPOSE

Stop smoking aid

DOSAGE AND ADMINISTRATION

reduces withdrawal symptoms, including nicotine craving, associated with quitting smoking.

WARNINGS

lf you are pregnant or breast-feeding, only use this medicine on the advice ofyour health care provider. Smoking can seriously harm your child. Try to stop smoking without using any nicotine replacement medicine. This medicine is believed to safer than smoking. However, the risks to your child from this medicine are not fully known.

ASK DOCTOR

If you have

- Heart disease, recent heart attack, or ireqular heartbeat, Nicotine can increase your heart rate.
- High blood pressurenot controlled with medication. Nicotine can increase your blood pressure.
- An allergy to adhesive tape or have skinproblems, because you are more likely to get rashes.
- Stomach ulcer or diabetes.
- History of seizures.

ASK DOCTOR/PHARMACIST

If you are

- Using a non-nicotine stop smoking drug
- Taking a prescription medicine for depression or asthma. Your prescription dose may need to be adjusted.

WHEN USING

If you have vivid dreams or other sleep disturbances, remove this patch at bedtime.

STOP USE

- Skin redness caused by the patch does not go away after four days, or if your skin swells, or you get a rash.
- Irregular heartbeat or palpitations occur
- You get symptoms of nicotine overdose, such as nausea, vomiting, dizziness, weakness and rapid heartbeat.
- You have symptoms of an allergic reaction (such as diffculty breathing or rash)

KEEP OUT OF REACH OF CHILDREN

Used patches have enough nicotine to poison children and pets. lf swallowed, get medical help or contact a Poison Control Center right away. Save pouch to use for patch disposal. Dispose of the usedpatches by folding sticky ends together and putting in pouch.

INDICATIONS AND USAGE

- if you are under 18 years of age, ask a doctor before use.
- before using this product, read the enclosed self help guidefor complete directions and other information
- begin using the patch on your quit day
- if you smoke more than 10cigarettes per day,
- use the following schedule below:

- lf you smoke 10 or less cigarettes per day, do not use Step 1(21 mg). Start with Step 2(14 mg) for 6 weeks, then Step3(7 mg) for 2 weeks and then stop.
- apply one new patch every 24 hours on skin that is dry, clean and hairless.
- removebacking from patch and immediately press onto skin. Hold for 10 seconds.
- wash hands after applying or removing patchSave pouch to use for patch disposal Dispose of the used patches by folding sticky ends together and putting in pouch.
- the used patch should be removed and a new one applied to a different skin site at the same time each day.
- if you havevivid dreams, you may remove the patch at bedtime and apply a new one in the morning.
- you may wear the patch for 18to 24 hours
- do not wear more than one patch at a time
- do not cut patch in half or into smaller pieces
- do not leavepatch on for more than 24 hours because if may irritate your skin and loses strength after 24 hours
- to avoid possibleburns, remove patch before underaoing and MRllmaanetic resonance imaging) procedures
- it is important to complete treatment. lf you feel you need to use the patch for a longer period to keep from smoking, talk to your health care provider.

INACTIVE INGREDIENT

CODONOPSIS PILOSULA ROOT, CHRYSANTHEMUM INDICUM FLOWER,CLOVE LEAF OIL,TOBACCO LEAF, CAMPHOR OIL